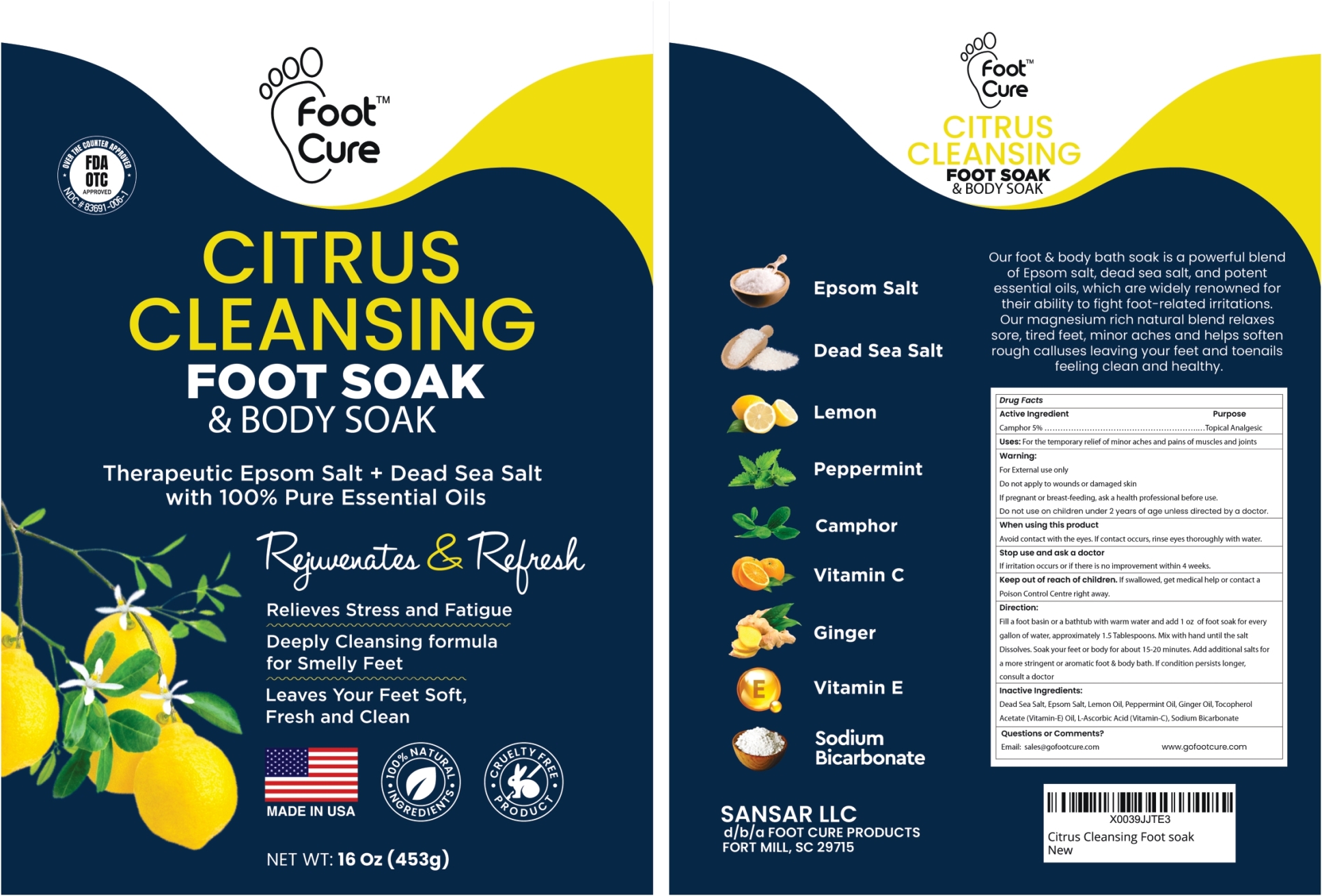 DRUG LABEL: Citrus Cleansing Foot Soak and Body Soak
NDC: 83691-006 | Form: GRANULE
Manufacturer: SANSAR, LLC
Category: otc | Type: HUMAN OTC DRUG LABEL
Date: 20250328

ACTIVE INGREDIENTS: CAMPHOR (NATURAL) 5 g/100 g
INACTIVE INGREDIENTS: SEA SALT; MAGNESIUM SULFATE HEPTAHYDRATE; LEMON OIL, COLD PRESSED; PEPPERMINT OIL; GINGER OIL; .ALPHA.-TOCOPHEROL ACETATE; ASCORBIC ACID; SODIUM BICARBONATE

Citrus Cleansing Foot Soak and Body Soak

Active Ingredient

Camphor 5%

Purpose

Topical Analgesic

Uses

For the temporary relief of minor aches and pains of muscles and joints

Warning

For External use only
Do not apply to wounds or damaged skin
If pregnant or breast-feeding, ask a health professional before use.
Do not use on children under 2 years of age unless directed by a doctor.

When using this product Avoid contact with the eyes. If contact occurs, rinse eyes thoroughly with water.

Stop use and ask a doctor If irritation occurs or if there is no improvement within 4 weeks.

Keep out of reach of children. If swallowed, get medical help or contact a Poison Control Centre right away.

Direction

Fill a foot basin or a bathtub with warm water and add 1 oz of foot soak for every gallon of water, approximately 1.5 Tablespoons. Mix with hand until the salt Dissolves. Soak your feet or body for about 15-20 minutes. Add additional salts for a more stringent or aromatic foot & body bath. If condition persists longer, consult a doctor.

Inactive Ingredients

Dead Sea Salt, Epsom Salt, Lemon Oil, Peppermint Oil, Ginger Oil, Tocopherol Acetate (Vitamin-E) Oil, L-Ascorbic Acid (Vitamin-C), Sodium Bicarbonate

Questions or Comments?

Email: sales@gofootcure.com or www.gofootcure.com